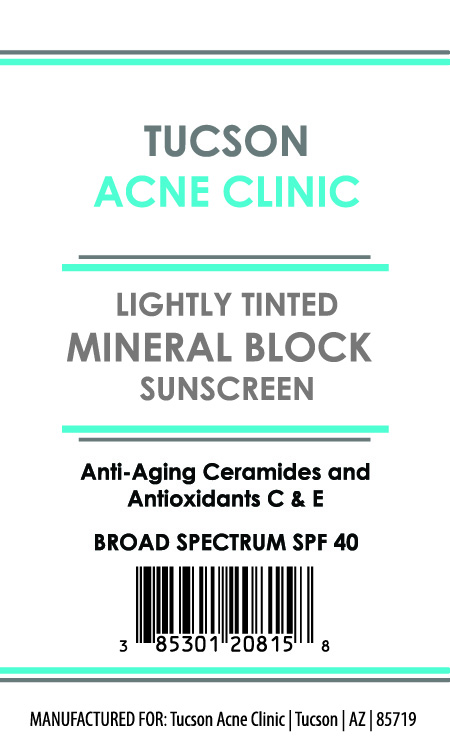 DRUG LABEL: Lightly Tinted Mineral Block Sunscreen
NDC: 85301-208 | Form: CREAM
Manufacturer: Tucson Acne Clinic
Category: otc | Type: HUMAN OTC DRUG LABEL
Date: 20251209

ACTIVE INGREDIENTS: ZINC OXIDE 160 mg/1 g
INACTIVE INGREDIENTS: DIMETHICONE/VINYL DIMETHICONE CROSSPOLYMER (SOFT PARTICLE); CI 77499; CYCLOHEXASILOXANE; PEG-10 DIMETHICONE (600 CST); CAPRYLIC/CAPRIC TRIGLYCERIDE; HYDROGEN DIMETHICONE (20 CST); POLYHYDROXYSTEARIC ACID (2300 MW); CYCLOPENTASILOXANE; DIMETHICONOL (2000 CST); CI 77492; CI 77491; TETRAHEXYLDECYL ASCORBATE; CERAMIDE 3; DIMETHICONE CROSSPOLYMER; DIMETHICONE; ALPHA-TOCOPHEROL ACETATE; VINYL DIMETHICONE/METHICONE SILSESQUIOXANE CROSSPOLYMER

Active Ingredients:

Zinc Oxide 16%

Purpose:

Sunscreen

Warning:

For external use only

Warning:

For external use only

Keep out of reach of children

Directions:

Apply liberally 15 minutes before sun exposure

INACTIVE INGREDIENT

Capric/Caprylic Triglyceride, Ceramide 3, Cyclohexasiloxane, Cyclopentasiloxane, Dimethicone, Dimethicone Crosspolymer, Dimethicone/Vinyl Dimethicone Crosspolymer, Dimethiconol, Iron Oxide, Hydrogen Dimethicone, PEG-10 Dimethicone, Polyhydroxystearic Acid, Tetrahexyldecyl Ascorbate, Tocopheryl Acetate, Vinyl Dimethicone/Methicone Silsesquioxane Crosspolymer

OTHER SAFETY INFORMATION

SAMPLE NOT FOR RESALE

Warning:

Keep out of reach of children